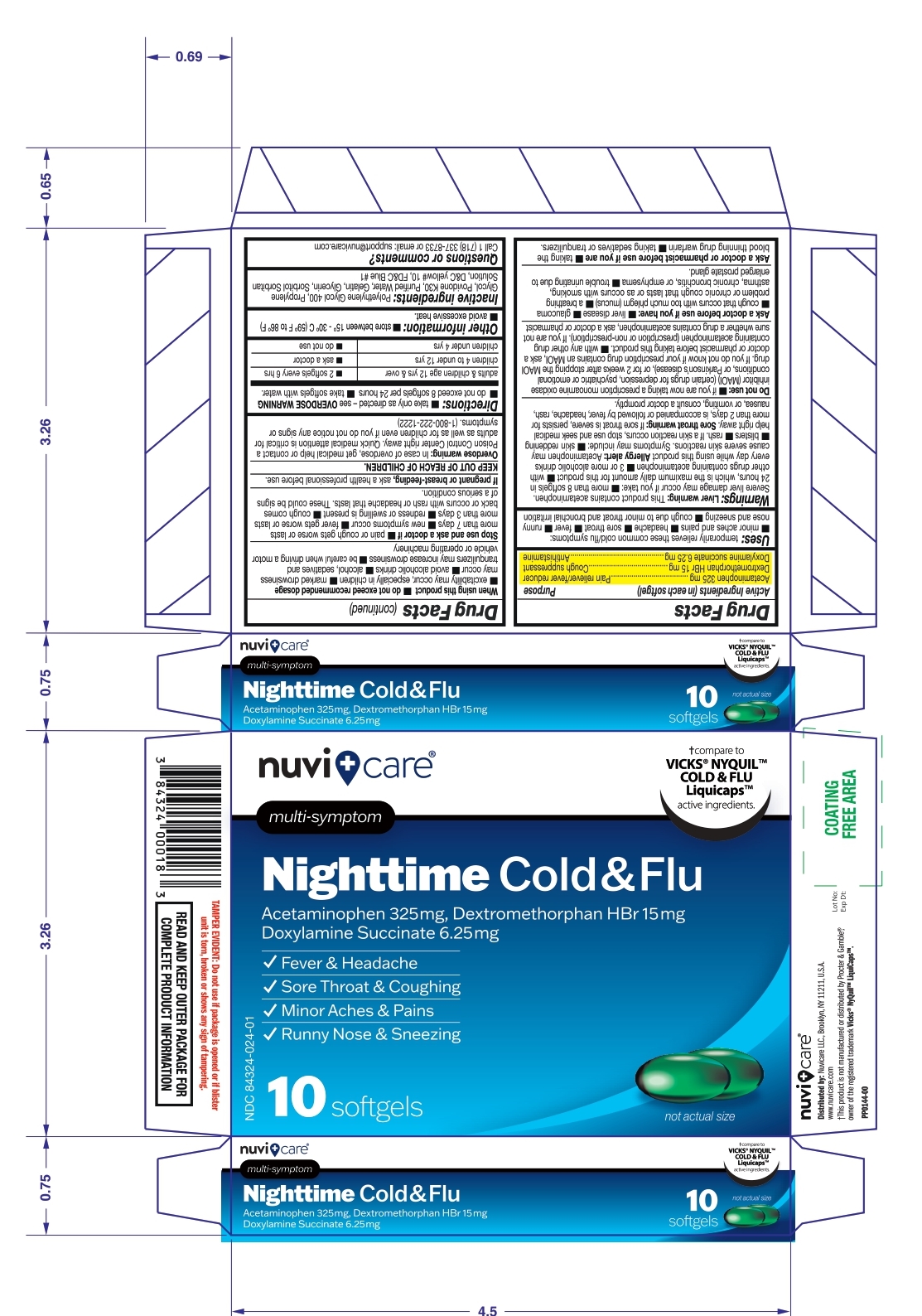 DRUG LABEL: Nuvicare NightTime Cold and Flu Softgel
NDC: 84324-024 | Form: CAPSULE, LIQUID FILLED
Manufacturer: NUVICARE LLC
Category: otc | Type: HUMAN OTC DRUG LABEL
Date: 20250609

ACTIVE INGREDIENTS: ACETAMINOPHEN 325 mg/1 1; DEXTROMETHORPHAN HYDROBROMIDE 15 mg/1 1; DOXYLAMINE SUCCINATE 6.25 mg/1 1
INACTIVE INGREDIENTS: POLYETHYLENE GLYCOL 400; PROPYLENE GLYCOL; POVIDONE; WATER; Gelatin; Sorbitol; SORBITAN; GLYCERIN; FD&C BLUE NO. 1; D&C YELLOW NO. 10

Nuvicare NightTime Cold and Flu Softgel (Acetaminophen 325mg, Dextromethorphan HBr 15mg, Doxylamine succinate 6.25 mg)

Active ingredients (in each softgel)

Acetaminophen 325mg

Dextromethorphan HBr 15mg

Doxylamine succinate 6.25 mg

Purpose

Acetaminophen 325mg.....................Pain reliever/fever reducer
Dextromethorphan HBr 15mg..................... Cough suppressant
Doxylamine succinate 6.25 mg ............................. Antihistamine

Uses:

temporarily relieves these common cold/flu symptoms:
■ minor aches & pains

■ headache

■ sore throat

■ fever

■ Runny nose and sneezing

■ cough due to minor throat & bronchial irritation

Warning

Liver warning: This product contains acetaminophen. Severe liver damage may occur if you take:
■ more than 8 softgels in 24 hours, which is the maximum daily amount for this product ■ with other drugs containing acetaminophen ■ 3 or more alcoholic drinks everyday while using this product.

Allergy Alert: acetamenophen may cause severe skin recations. Symptoms may include:

■ skin reddening ■ blisters ■ rash. if a skin reactions occurs, stop use and seek medical help right away.

Sore throat warning: If sore throat is severe, persists for more than 2 days, is accompanied or followed by fever, headache, rash, nausea, or vomiting,consult a doctor promptly.

Do not use:

- if you are now taking a prescription monoamine oxidase inhibitor (MAOI) (certain drugs for depression, psychiatric or emotional conditions, or Parkinson's disease), or for 2 weeks after stopping the MAOI drug. If you do not know if your prescription drug contains an MAOI, ask a doctor or pharmacist before taking this product.
- with any other drug containing acetaminophen (prescription or nonprescription). If you are not sure whether a drug contains acetaminophen, ask a doctor or pharmacist

Ask a doctor before use if you have

■ liver disease

■ glaucoma

■ cough that occurs with too much phlegm (mucus)

■ a breathing problem or chronic cough that last or as occurs with smoking, asthma, chronic bronchitis, or emphysema

■ trouble urinating due to enlarged prostate gland

Ask a doctor or pharmacist before use if you are

- taking the blood thinning drug warfarin
- taking sedative or tranquilizers.

When using this product

- do not exceed recommeded dosage.
- excitability may occur, especially in children
- marked drowsiness may occur
- avoid alcoholic drinks
- alcohol, sedative and tranquilizers may increase drowsiness
- be careful when driving a motor vehicle or operating machinery

Stop use and ask a doctor if

- pain or cough get worse or lasts more than 7 days
- new symptoms occur
- fever gets worse or lasts more than 3 days
- redness or swelling is present
- cough comes back or occurs with rash or headache that lasts. These could be signs of a serious condition.

PREGNANCY OR BREAST FEEDING

If pregnant or breast-feeding, ask a health professional before use.

Keep out of reach of children.

OVERDOSAGE

Overdose warning: In case of overdose, get medical help or contact a Poison Control Center right away. Quick medical attention is critical for adults as well as for children even if you do not notice any signs or symptoms. (1-800-222-1222)

Directions

■ take only as directed- see OVERDOSE WARNING

■ do not exceed 8 softgels per 24 hrs.

■ take softgels with water

Adults and children age 12 yrs and over | 2 softgels every 6 hrs.
Children 4 to under 12 yrs | ask a doctor
Children under 4 yrs | do not use

Other information

■ store between 15-30°C (59 to 86 °F)

■ avoid excessive heat

Inactive ingredients

Polyethylene Glycol400, Propylene Glycol, Povidone K-30,Purified water, Gelatin, Glycerin, Sorbitol Sorbitan solution, FD & C Blue No. 1, D &C Yellow No.10

Questions or Comments?

Call 1-718-337-8733 or email: support@nuvicare.com

Distributed by: Nuvicare LLC, Brooklyn, NY 11211, USA